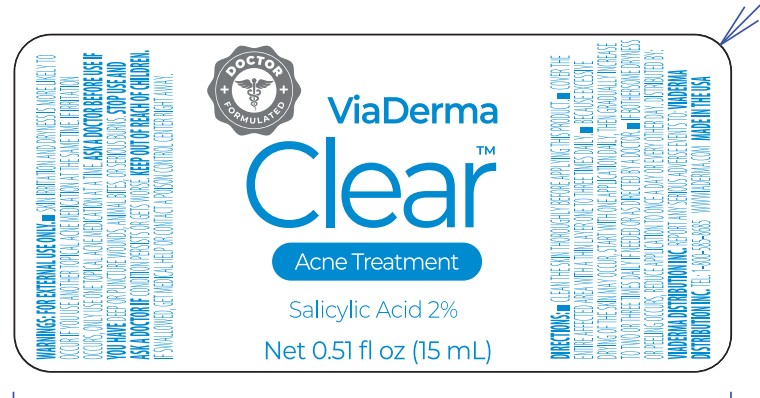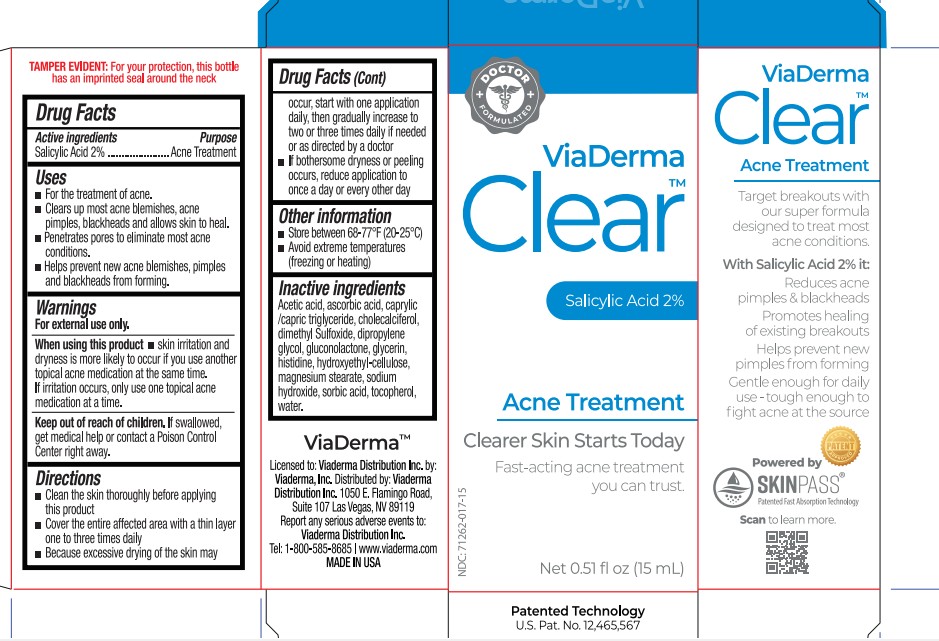 DRUG LABEL: Viaderma Clear Acne Treatment
NDC: 71262-017 | Form: SOLUTION
Manufacturer: VIADERMA DISTRIBUTION INC
Category: otc | Type: HUMAN OTC DRUG LABEL
Date: 20260127

ACTIVE INGREDIENTS: SALICYLIC ACID 20 mg/1 mL
INACTIVE INGREDIENTS: ACETIC ACID; MEDIUM-CHAIN TRIGLYCERIDES; CHOLECALCIFEROL; DIMETHYL SULFOXIDE; DIPROPYLENE GLYCOL; GLUCONOLACTONE; GLYCERIN; HISTIDINE; HYDROXYETHYL CELLULOSE, UNSPECIFIED; MAGNESIUM STEARATE; SODIUM HYDROXIDE; SORBIC ACID; STEARIC ACID; TETRAHEXYLDECYL ASCORBATE; TOCOPHEROL; WATER

Viaderma Clear Acne Treatment

Active ingredient

Salicylic Acid 2%

Purpose

Acne Treatment

Uses

- For the treatment of acne.
- Clears up most acne blemishes, acne pimples, blackheads and allows skin to heal.
- Penetrates pores to eliminate most acne conditions.
- Hepls prevent new acne blemishes, pimples and blackheads from forming.

Warnings

For external use only.

When using this product

- skin irritation and dryness is more likely to occur if you use another topical acne medication at the same time. If irritation occurs, only use one topical acne medication at a time.

Keep out of reach of children.

If swallowed, get medical help or contact a Poison Control Center right away.

Directions

- Clean the skin thoroughly before applying this product
- Cover the entire affected area with a thin layer one to three times daily
- Because excessive drying of the skin may

Other information

- store between 68-77°F (20-25°C)
- Avoid extreme temperatures (freezing or heating)

Inactive ingredients

Acetic acid, caprylic/capric triglyceride, cholecalciferol, dimethyl sulfoxide, dipropylene glycol, gluconolactone, glycerin, histidine, hydroxyethyl-cellulose, magnesium stearate, sodium hydroxide, sorbic acid, stearic acid, tetrahexyldecyl ascorbate, tocopherol, water.